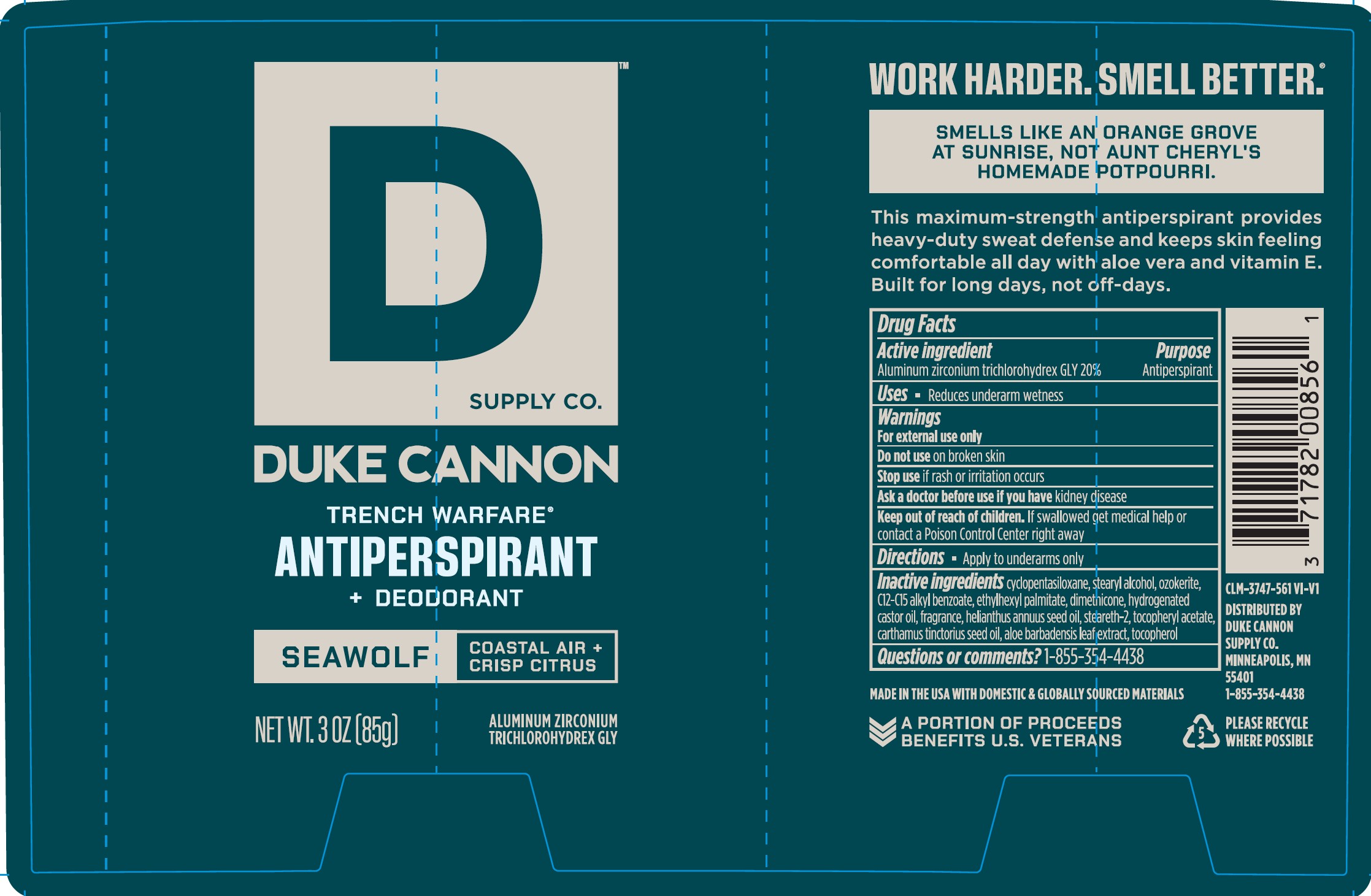 DRUG LABEL: Trench Warfare Antiperspirant Deodorant Seawolf
NDC: 71782-305 | Form: STICK
Manufacturer: Duke Cannon Supply Co.
Category: otc | Type: HUMAN OTC DRUG LABEL
Date: 20251201

ACTIVE INGREDIENTS: ALUMINUM ZIRCONIUM TRICHLOROHYDREX GLY 20 g/100 g
INACTIVE INGREDIENTS: CERESIN; STEARETH-2; DIMETHICONE; HYDROGENATED CASTOR OIL; SAFFLOWER OIL; STEARYL ALCOHOL; TOCOPHEROL; CYCLOMETHICONE 5; ALPHA-TOCOPHEROL ACETATE; SUNFLOWER OIL; ALOE VERA LEAF; ALKYL (C12-15) BENZOATE; ETHYLHEXYL PALMITATE

Trench Warfare Antiperspirant Deodorant Seawolf

Drug Facts

Active ingredient

Aluminum zirconium trichlorohydrex GLY 20%

Purpose

Antiperspirant

Uses

reduces underam wetness

Warnings

For external use only

Do not use

on broken skin

Stop use

if rash or irritation occurs

Ask a doctor before use

if you have kidney disease

Keep out of reach of children.If swallowed get medical help or contact a Poison Control Center right away.

Directions

apply to underarms only

Inactive ingredients

cyclopentasiloxane, stearyl alcohol, ozokerite, C12-C15 alkyl benzoate, ethylhexyl palmitate, dimethicone, hydrogenated castor oil, fragrance, helianthus annuus seed oil, steareth-2, tocopheryl acetate, cartamus tinctorius seed oil, aloe barbadensis leaf extract, tocopherol

Questions or comments?

1-855-354-4438

Distributed by

Duke Cannon Supply Co.

Minneapolis, MN 55401

Principal Display Panel

DUKE CANNON

Trench Warfare

Antiperspirant

+ Deodorant

SEAWOLF | Coastal Air + Crisp Citrus

Net Wt. 3 oz (85g)

Aluminum Zirconium Trichlorohydrex GLY